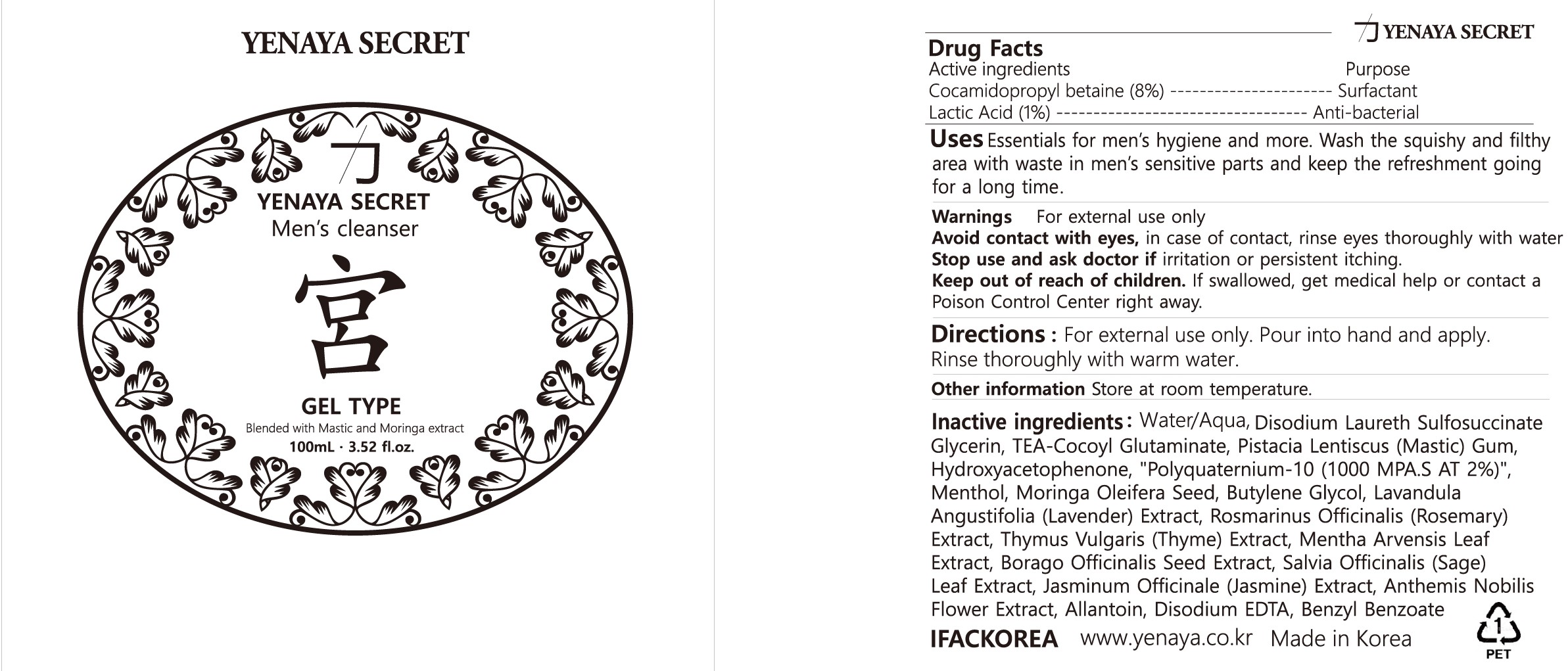 DRUG LABEL: YENAYA SECRET GUNG CLEANSER
NDC: 81873-201 | Form: GEL
Manufacturer: IFACKOREA CO., LTD
Category: otc | Type: HUMAN OTC DRUG LABEL
Date: 20231226

ACTIVE INGREDIENTS: COCAMIDOPROPYL BETAINE 8 mg/100 mL; LACTIC ACID, UNSPECIFIED FORM 1 mg/100 mL
INACTIVE INGREDIENTS: ORANGE OIL; CHAMAEMELUM NOBILE FLOWER; .ALPHA.-HEXYLCINNAMALDEHYDE; BENZYL SALICYLATE; METHYL DIHYDROJASMONATE (SYNTHETIC); PHENYLETHYL ALCOHOL; EDETATE DISODIUM ANHYDROUS; MENTHOL, UNSPECIFIED FORM; BUTYLPHENYL METHYLPROPIONAL; WATER; DISODIUM LAURETH SULFOSUCCINATE; ALLANTOIN; TRIETHANOLAMINE COCOYL GLUTAMINATE; BORAGO OFFICINALIS SEED; SAGE; ROSEMARY; GLYCERIN; BUTYLENE GLYCOL; POLYQUATERNIUM-10 (1000 MPA.S AT 2%); PISTACIA LENTISCUS RESIN OIL; HYDROXYACETOPHENONE; MORINGA OLEIFERA SEED OIL; LAVANDULA ANGUSTIFOLIA SUBSP. ANGUSTIFOLIA FLOWERING TOP; THYME; MENTHA ARVENSIS LEAF; JASMINUM OFFICINALE FLOWER

81873-201 YENAYA SECRET GUNG CLEANSER

Active ingredients

Cocamidopropyl betaine (8%)
Lactic Acid (1%)

Purpose

Surfactant

Anti-bacterial

Uses

Essentials for men’s hygiene and more. Wash the squishy and filthy area with waste in men’s sensitive parts and keep the refr eshment going for a long time.

Warnings

For external use only

When using section

Avoid contact with eyes, in case of contact, rinse eyes thoroughly with wather.

Stop use and ask doctor if

irritation or persistent itching.

Keep out of reach of children

If swallowed, get medical help or contact a Poison Control Center right away.

Directions

Pour into hand and apply. Rinse thoroughly with warm water.

Other information

Store at room temperature

Inactive ingredients

Water (Aqua), Dis odium Laureth Sulfa te, Glycerin, TEA Cocoyl Glutaminate, Pistacia Lentiscus (Mastic) Gum, Hydroxyace
tophenone, “Polyquaternium 10(1000 MPA.S AT 2%)”, Menthol, Moringa Oleifera Seed, Butylene Glycol, Angustifolia (Lavender) Extract, Rosmarinus Officinalis (Rosemary) Extract, Thymus Vulgaris (Thyme) Extract, Mentha Arvensis Leaf Extract, Borago Officinaris Seed Extract, Salvia Officinalis (Sage) Leaf Extract, Jasminum Officinale (Jasmine) Extract, Anthemis Nobilis Flower Extract, Allantoin, Disodium EDTA, Benzyl Benzoate.